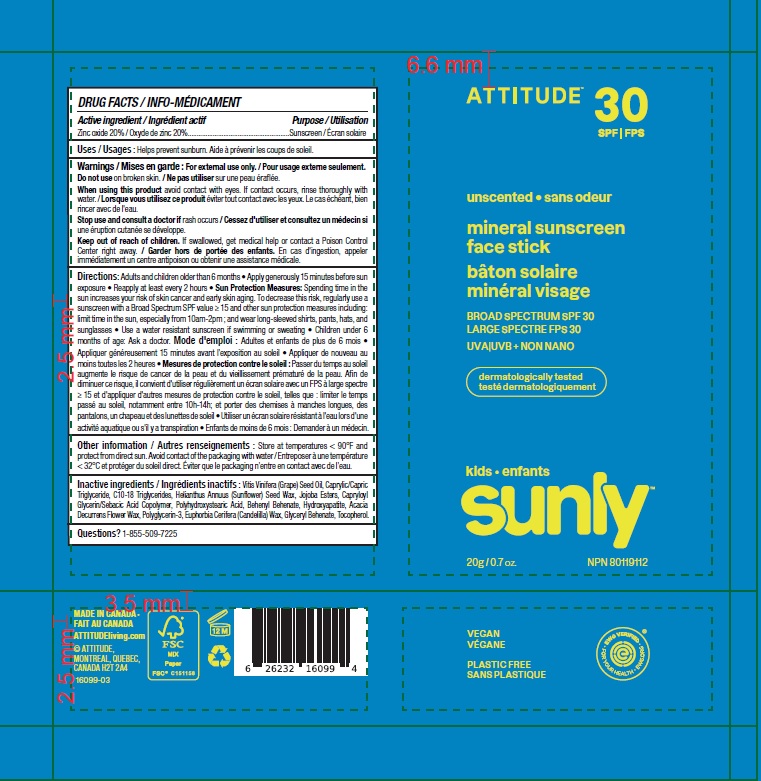 DRUG LABEL: ATTITUDE Sunly Kids Mineral Sunscreen Face Stick Unscented SPF 30
NDC: 61649-099 | Form: STICK
Manufacturer: 9055-7588 Quebec Inc. DBA Attitude
Category: otc | Type: HUMAN OTC DRUG LABEL
Date: 20241209

ACTIVE INGREDIENTS: ZINC OXIDE 20 g/100 g
INACTIVE INGREDIENTS: MEDIUM-CHAIN TRIGLYCERIDES; JOJOBA OIL; ACACIA DECURRENS FLOWER WAX; CAPRYLOYL GLYCERIN/SEBACIC ACID COPOLYMER (2000 MPA.S); GRAPE SEED OIL; C10-18 TRIGLYCERIDES; POLYHYDROXYSTEARIC ACID (2300 MW); BEHENYL BEHENATE; TRIBASIC CALCIUM PHOSPHATE; HELIANTHUS ANNUUS SEED WAX; POLYGLYCERIN-3; CANDELILLA WAX; GLYCERYL MONOBEHENATE; .ALPHA.-TOCOPHEROL

ATTITUDE Sunly Kids Mineral Sunscreen Face Stick - Unscented - SPF 30

DRUG FACTS

ACTIVE INGREDIENT

Zinc oxide (20 %)

PURPOSE

Sunscreen

INDICATIONS AND USAGE

Helps prevent sunburn.

WARNINGS

For external use only.

Do not use on broken skin.

When using this product avoid contact with eyes. If contact occurs, rinse thoroughly with water.

Keep out of reach of children. If swallowed, get medical help or contact a Poison Control Center right away.

Stop use and consult a doctor if rash occurs.

DOSAGE AND ADMINISTRATION

Adults and children older than 6 months.

- Apply generously 15 minutes before sun exposure.
- Reapply at least every 2 hours.
- Sun Protection Measures: Spending time in the sun increases your risk of skin cancer and early aging. To decrease this risk, regularly use a sunscreen with a Broad Spectrum SPFvalue of 15 or higher and other sun protection measures including: limit time in the sun, especially from 10am-2pm; and wear long-sleeved shirts, pants, hats and sunglasses.
- Use a water resistant sunscreen if swimming or sweating.
- Children under 6 months of age: Ask a doctor.

STORAGE AND HANDLING

Store at temperatures < 90F and protect from direct sun. Avoid contact of packaging with water.

INACTIVE INGREDIENT

Vitis Vinifera (Grape) Seed Oil, Caprylic/Capric Triglyceride, C10-18 Triglycerides, Helianthus Annuus (Sunflower) Seed Wax, Jojoba Esters, Capryloyl Glycerin/Sebacic Acid Copolymer, Polyhydroxystearic Acid, Behenyl Behenate, Hydroxyapatite, Acacia Decurrens Flower Wax, Polyglycerin-3, Euphorbia Cerifera (Candelilla) Wax, Glyceryl Behenate, Tocopherol.

Questions ? 1-855-509-7225

PACKAGE LABEL

ATTITUDE

natural care

SPF 30

unscented

mineral sunscreen face stick

BROAD SPECTRUM SPF 30

UVA UVB + NON NANO

Kids

SUNLY Plastic Free Suncare

20 g / 0.7 oz.

NPN 80119112

Vegan

EWG Verified

Ocean Lovers

Plastic Free

Dermatologically tested